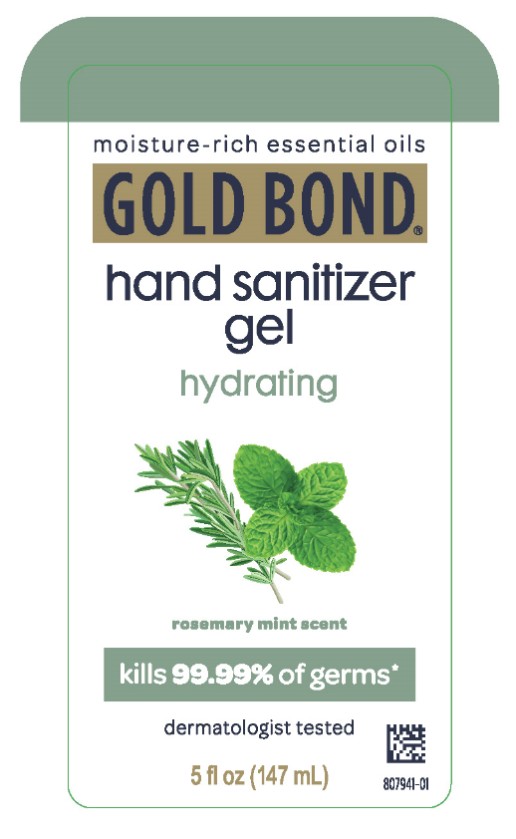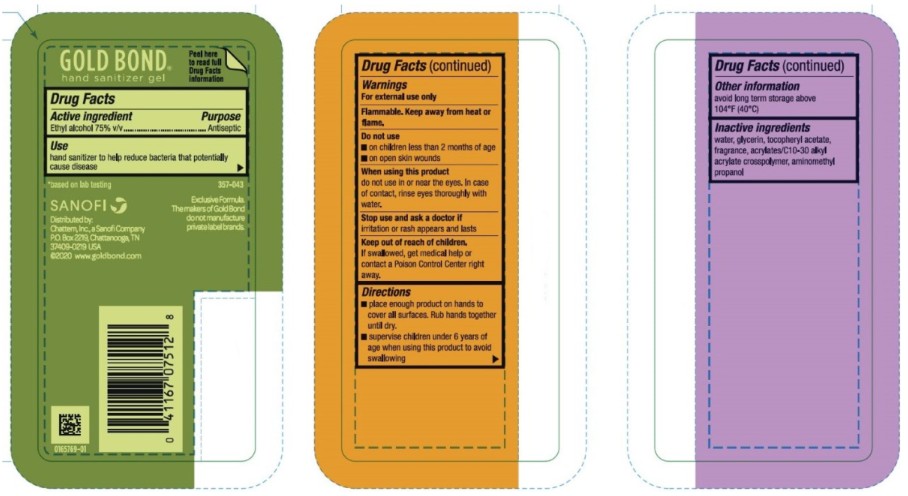 DRUG LABEL: Gold Bond Hydrating Hand Sanitizer
NDC: 41167-0751 | Form: GEL
Manufacturer: Chattem, Inc.
Category: otc | Type: HUMAN OTC DRUG LABEL
Date: 20260114

ACTIVE INGREDIENTS: ALCOHOL 75 mL/100 mL
INACTIVE INGREDIENTS: WATER; GLYCERIN; .ALPHA.-TOCOPHEROL ACETATE; CARBOMER INTERPOLYMER TYPE A (55000 CPS); AMINOMETHYLPROPANOL

Gold Bond Hydrating Hand Sanitizer Gel

Gold Bond® Hydrating Hand Sanitizer Gel

Drug Facts

Active ingredient

Ethyl alcohol 75% v/v

Purpose

Antiseptic

Use

hand sanitizer to help reduce bacteria that potentially cause disease

Warnings

For external use only

Flammable. Keep away from heat or flame.

Do not use

■ on children less than 2 months of age

■ on open skin wounds

When using this product

do not use in or near the eyes. In case of contact, rinse eyes thoroughly with water.

Stop use and ask a doctor if

irritation or rash appears and lasts

Keep out of reach of children.

If swallowed, get medical help or contact a Poison Control Center right away.

Directions

■ place enough product on hands to cover all surfaces. Rub hands together until dry.

■ supervise children under 6 years of age when using this product to avoid swallowing

Other information

avoid long term storage above 104°F (40°C)

Inactive ingredients

water, glycerin, tocopheryl acetate, fragrance, acrylates/C10-30 alkyl acrylate crosspolymer, aminomethyl propanol

PRINCIPAL DISPLAY PANEL

Moisture-rich essential oils
GOLD BOND
hand sanitizer
gel
hydrating
rosemary mint scent
5 fl oz (147 mL)